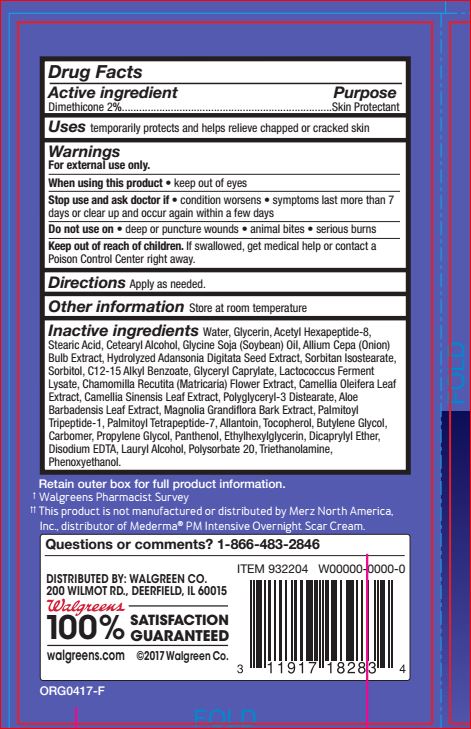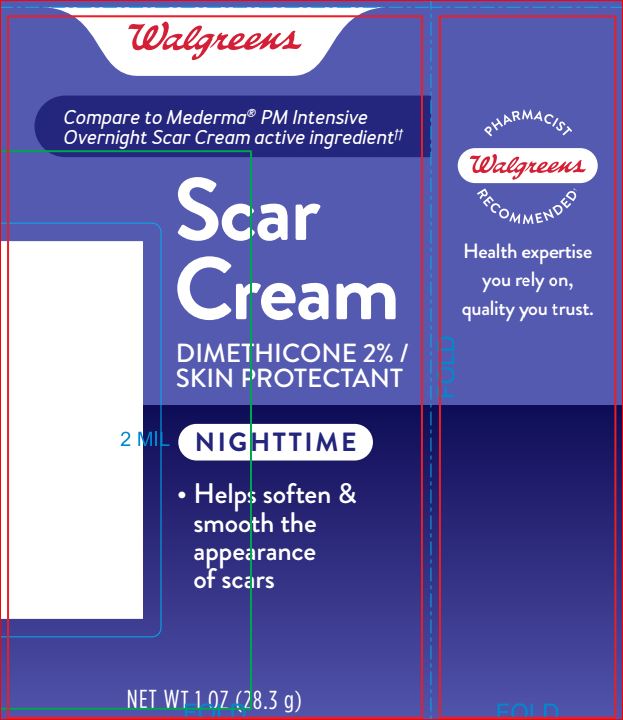 DRUG LABEL: Scar
NDC: 0363-1118 | Form: CREAM
Manufacturer: Walgreens
Category: otc | Type: HUMAN OTC DRUG LABEL
Date: 20180413

ACTIVE INGREDIENTS: DIMETHICONE 2 g/100 g
INACTIVE INGREDIENTS: Acetyl Hexapeptide-8; Allantoin; ONION; ALOE VERA LEAF; Butylene Glycol; ALKYL (C12-15) BENZOATE; CAMELLIA OLEIFERA LEAF; GREEN TEA LEAF; CARBOMER HOMOPOLYMER TYPE C (ALLYL PENTAERYTHRITOL CROSSLINKED); CETOSTEARYL ALCOHOL; CHAMOMILE; Dicaprylyl Ether; EDETATE DISODIUM ANHYDROUS; Ethylhexylglycerin; Glycerin; Glyceryl Caprylate; SOYBEAN OIL; Lauryl Alcohol; MAGNOLIA GRANDIFLORA BARK; Palmitoyl Tetrapeptide-7; Palmitoyl Tripeptide-1; Panthenol; Phenoxyethanol; Polyglyceryl-3 Distearate; Polysorbate 20; Propylene Glycol; Sorbitan Isostearate; Sorbitol; Stearic Acid; Tocopherol; TROLAMINE; Water

Drug Facts

Active ingredient Purpose
Dimethicone 2%.......................................Skin Protectant

INDICATIONS AND USAGE

Uses temporarily protects and helps relieve chapped or cracked skin

Warnings
For external use only.
When using this product • keep out of eyes
Stop use and ask doctor if • condition worsens • symptoms last more than 7
days or clear up and occur again within a few days
Do not use on • deep or puncture wounds • animal bites • serious burns
Keep out of reach of children. If swallowed, get medical help or contact a Poison Control Center right away.

DOSAGE AND ADMINISTRATION

Directions Apply as needed

Inactive ingredients Water, Glycerin, Acetyl Hexapeptide-8,
Stearic Acid, Cetearyl Alcohol, Glycine Soja (Soybean) Oil, Allium Cepa (Onion)
Bulb Extract, Hydrolyzed Adansonia Digitata Seed Extract, Sorbitan Isostearate,
Sorbitol, C12-15 Alkyl Benzoate, Glyceryl Caprylate, Lactococcus Ferment
Lysate, Chamomilla Recutita (Matricaria) Flower Extract, Camellia Oleifera Leaf
Extract, Camellia Sinensis Leaf Extract, Polyglyceryl-3 Distearate, Aloe
Barbadensis Leaf Extract, Magnolia Grandiflora Bark Extract, Palmitoyl
Tripeptide-1, Palmitoyl Tetrapeptide-7, Allantoin, Tocopherol, Butylene Glycol,
Carbomer, Propylene Glycol, Panthenol, Ethylhexylglycerin, Dicaprylyl Ether,
Disodium EDTA, Lauryl Alcohol, Polysorbate 20, Triethanolamine,
Phenoxyethanol.